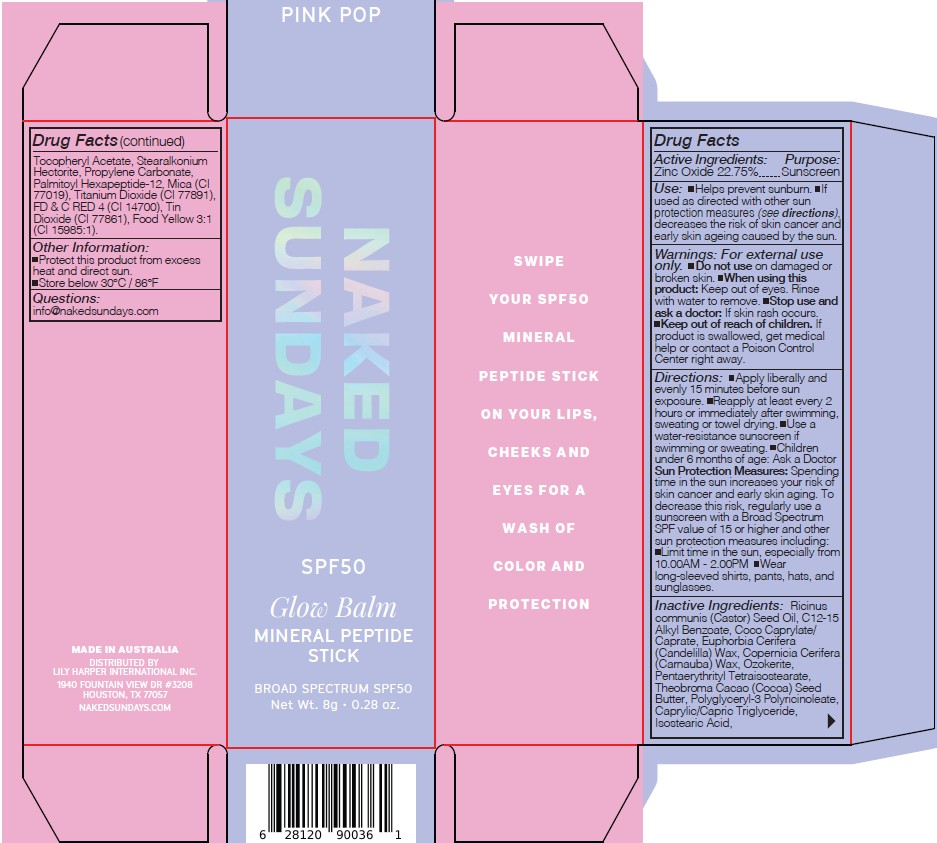 DRUG LABEL: Naked Sundays Glow Balm Mineral Peptide Stick Broad Spectrum SPF50 Pink Pop 8g
NDC: 81104-106 | Form: STICK
Manufacturer: NAKED SUNDAYS PTY LTD
Category: otc | Type: HUMAN OTC DRUG LABEL
Date: 20251114

ACTIVE INGREDIENTS: ZINC OXIDE 22.75 g/100 g
INACTIVE INGREDIENTS: PROPYLENE CARBONATE; CI 14700; TIN OXIDE; STEARALKONIUM HECTORITE; MICA; POLYGLYCERYL-3 PENTARICINOLEATE; CAPRYLIC/CAPRIC TRIGLYCERIDE; EUPHORBIA CERIFERA (CANDELILLA) WAX; TITANIUM DIOXIDE; PENTAERYTHRITYL TETRAISOSTEARATE; THEOBROMA CACAO (COCOA) SEED BUTTER; C12-15 ALKYL BENZOATE; FD&C YELLOW NO. 6 ALUMINUM LAKE; PALMITOYL HEXAPEPTIDE-12; ISOSTEARIC ACID; .ALPHA.-TOCOPHEROL ACETATE; COCO-CAPRYLATE/CAPRATE; COPERNICIA CERIFERA (CARNAUBA) WAX; RICINUS COMMUNIS (CASTOR) SEED OIL; CERESIN

Naked Sundays Glow Balm Mineral Peptide Stick Broad Spectrum SPF50 Pink Pop 8g

ACTIVE INGREDIENT

Zinc Oxide 22.75%

PURPOSE

SPF Suncscreen

INDICATIONS AND USAGE

Use: Helps prevent sunburn. If
used as directed with other sun
protection measures (see directions),
decreases the risk of skin cancer and
early skin ageing caused by the sun.

Keep out of reach of children

DOSAGE AND ADMINISTRATION

Directions: Apply liberally and
evenly 15 minutes before sun
exposure. Reapply at least every 2
hours or immediately after swimming,
sweating or towel drying. Use a
water-resistance sunscreen if
swimming or sweating. Children
under 6 months of age: Ask a Doctor

OTHER SAFETY INFORMATION

Sun Protection Measures: Spending
time in the sun increases your risk of
skin cancer and early skin aging. To
decrease this risk, regularly use a
sunscreen with a Broad Spectrum
SPF value of 15 or higher and other
sun protection measures including:
Limit time in the sun, especially from
10.00AM - 2.00PM Wear
long-sleeved shirts, pants, hats, and
sunglasses.

Warnings: For external use
only. Do not use on damaged or
broken skin. When using this
product: Keep out of eyes. Rinse
with water to remove. Stop use and
ask a doctor: If skin rash occurs.
Keep out of reach of children. If
product is swallowed, get medical
help or contact a Poison Control
Center right away.

INACTIVE INGREDIENT

INACTIVE INGREDIENTS: C12-15 Alkyl Benzoate, Caprylic/Capric Triglyceride, Coco-Caprylate/Caprate, Copernicia Cerifera (Carnauba) Wax, Euphorbia Cerifera (Candelilla) Wax, FD&C Red No. 4 (CI 14700), FD&C Yellow 6 Lake (CI 15985:1), Isostearic Acid, Mica, Microcrystalline Wax, Palmitoyl Hexapeptide-12, Paraffin Wax, Pentaerythrityl Tetraisostearate, Polyglyceryl-3 Polyricinoleate, Propylene Carbonate, Ricinus Communis (Castor) Seed Oil, Stearalkonium Hectorite, Theobroma Cacao (Cocoa) Seed Butter, Tin Oxide, Titanium Dioxide (CI 77891), Tocopheryl Acetate